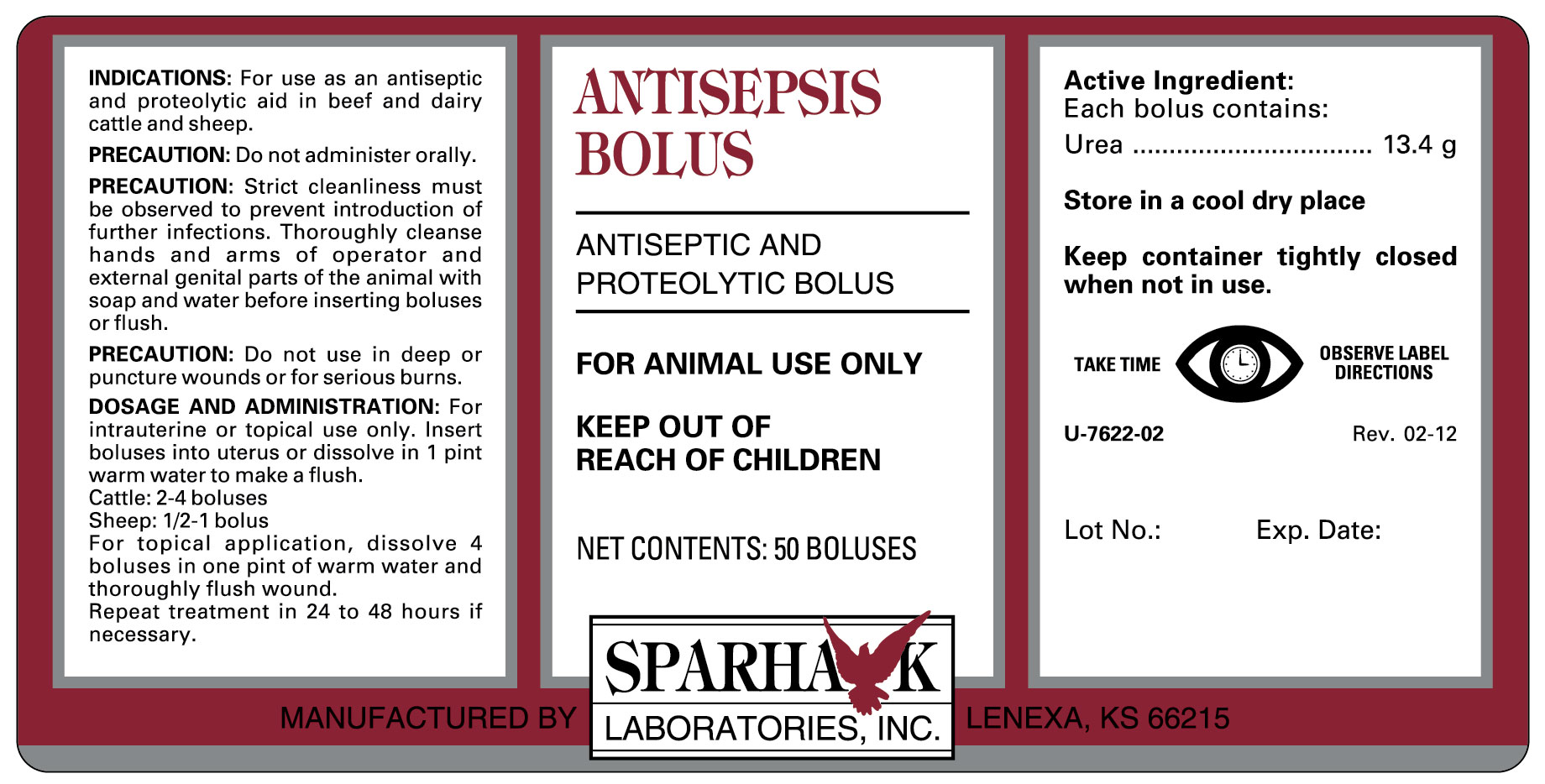 DRUG LABEL: ANTISEPSIS BOLUS
NDC: 58005-762 | Form: TABLET
Manufacturer: Sparhawk Laboratories, Inc.
Category: animal | Type: OTC ANIMAL DRUG LABEL
Date: 20140428

ACTIVE INGREDIENTS: UREA 13 g/1 1

ANTISEPSIS BOLUS

INDICATIONS AND USAGE

ANTISEPTIC AND PROTEOLYTIC BOLUS

FOR ANIMAL USE ONLY

KEEP OUT OF REACH OF CHILDREN

INDICATIONS

For use as an antiseptic and proteolytic aid in beef and dairy cattle and sheep.

PRECAUTION

Do not administer orally.

Strict cleanliness must be observed to prevent introduction of further infections. Thoroughly cleanse hands and arms of operator and external genital parts of the animal with soap and water before inserting boluses or flush.

Do not use in deep or puncture wounds or for serious burns.

DOSAGE AND ADMINISTRATION

For intrauterine or topical use only. Insert boluses into uterus or dissolve in 1 pint warm water to make a flush.
Cattle: 2-4 boluses
Sheep: 1/2-1 bolus
For topical application, dissolve 4 boluses in one pint of warm water and thoroughly flush wound.
Repeat treatment in 24 to 48 hours if necessary.

COMPOSITION

Each bolus contains: Urea, 13.4 g

STORAGE AND HANDLING

Store in a cool dry place; Keep container tightly closed when not in use.; TAKE TIME OBSERVE LABEL DIRECTIONS